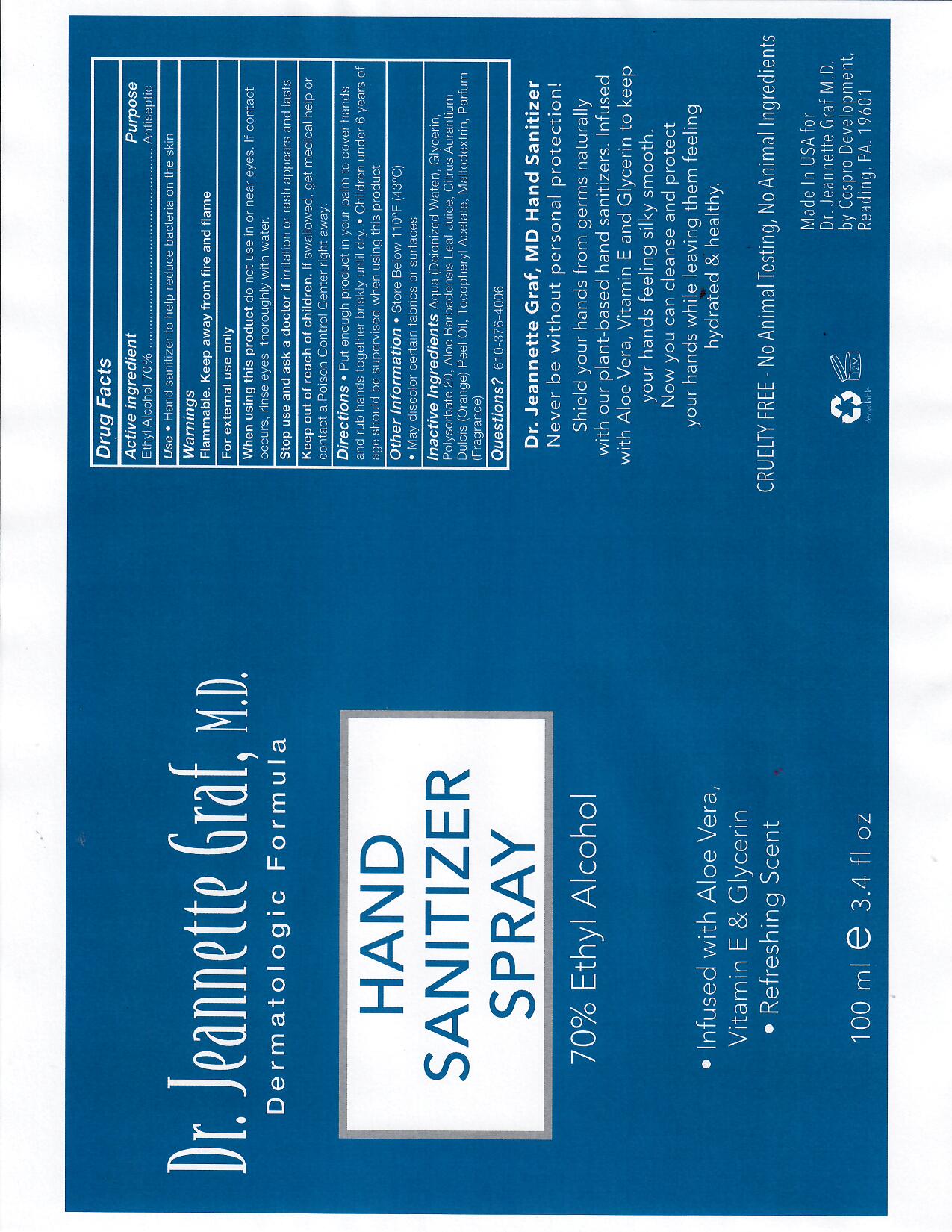 DRUG LABEL: DrGrafHandSanitizer
NDC: 46607-119 | Form: SOLUTION
Manufacturer: Cospro Development Corp
Category: otc | Type: HUMAN OTC DRUG LABEL
Date: 20200610

ACTIVE INGREDIENTS: ALCOHOL 70 mL/100 mL
INACTIVE INGREDIENTS: GLYCERIN; POLYSORBATE 20; WATER; ALOE; MALTODEXTRIN; ORANGE PEEL

This is a hand rub manufactured according to the Temporary Policy for Preparation of Certain Alcohol-Based Hand Rub Products During the Public Health Emergency (CoViD-19); Guidance for Industry.

The hand rub is manufactured using only the following United States Pharmacopoeia (USP) grade ingredients in the preparation of the product (percentage in final product formulation) consistent with World Health Organization (WHO) recommendations:

1. Alcohol (ethanol) (USP or Food Chemical Codex (FCC) grade) (70%, in an aqueous solution denatured according to Alcohol and Tobacco Tax and Trade Bureau regulations in 27 CFR part 20.
2. Glycerol.
3. Sterile distilled water.

Active Ingredient(s)

Alcohol 70%. Purpose: Antiseptic

Purpose

Antiseptic, Hand Rub

Use

Hand Sanitizer to help reduce bacteria on the skin

Warnings

For external use only. Flammable. Keep away from fire and flame

Do not use

- in or near eyes.

When using this product do not use in or near eyes. If contact occurs, rinse eyes thoroughly with water.
Stop use and ask a doctor if irritation or rash appears and lasts.
Keep out of reach of children. If swallowed, get medical help or contact a Poison Control Center right away.

Stop use and ask a doctor if irritation or rash appears and lasts.

Keep out of reach of children. If swallowed, get medical help or contact a Poison Control Center right away.

Directions

- Put enough product in your palm to cover hands and rub hands together briskly until dry.
- Children under 6 years of age should be supervised when using this product.

Other information

- Store below 110F (43C)

Inactive ingredients

deionized water, gylcerin, polysorbate 20, aloe barbadensis leaf juice, orange peel oil, tocopheryl acetate, maltodextrin, fragrance